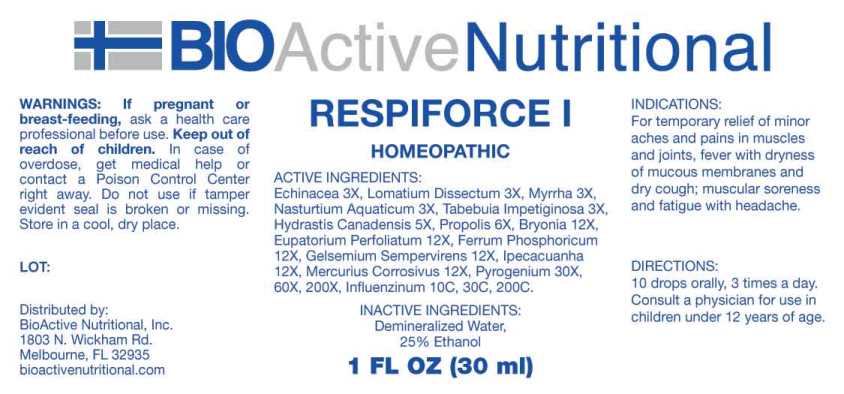 DRUG LABEL: Respiforce
NDC: 43857-0589 | Form: LIQUID
Manufacturer: BioActive Nutritional, Inc.
Category: homeopathic | Type: HUMAN OTC DRUG LABEL
Date: 20250516

ACTIVE INGREDIENTS: ECHINACEA ANGUSTIFOLIA WHOLE 3 [hp_X]/1 mL; LOMATIUM DISSECTUM ROOT 3 [hp_X]/1 mL; MYRRH 3 [hp_X]/1 mL; NASTURTIUM OFFICINALE 3 [hp_X]/1 mL; TABEBUIA IMPETIGINOSA BARK 3 [hp_X]/1 mL; GOLDENSEAL 5 [hp_X]/1 mL; PROPOLIS WAX 6 [hp_X]/1 mL; BRYONIA ALBA ROOT 12 [hp_X]/1 mL; EUPATORIUM PERFOLIATUM FLOWERING TOP 12 [hp_X]/1 mL; FERROSOFERRIC PHOSPHATE 12 [hp_X]/1 mL; GELSEMIUM SEMPERVIRENS ROOT 12 [hp_X]/1 mL; IPECAC 12 [hp_X]/1 mL; MERCURIC CHLORIDE 12 [hp_X]/1 mL; RANCID BEEF 30 [hp_X]/1 mL; INFLUENZA A VIRUS A/GUANGDONG-MAONAN/SWL1536/2019 CNIC-1909 (H1N1) ANTIGEN (FORMALDEHYDE INACTIVATED) 10 [hp_C]/1 mL; INFLUENZA A VIRUS A/HONG KONG/2671/2019 IVR-208 (H3N2) ANTIGEN (FORMALDEHYDE INACTIVATED) 10 [hp_C]/1 mL; INFLUENZA B VIRUS B/PHUKET/3073/2013 ANTIGEN (FORMALDEHYDE INACTIVATED) 10 [hp_C]/1 mL; INFLUENZA B VIRUS B/WASHINGTON/02/2019 ANTIGEN (FORMALDEHYDE INACTIVATED) 10 [hp_C]/1 mL
INACTIVE INGREDIENTS: WATER; ALCOHOL

DRUG FACTS:

ACTIVE INGREDIENTS:

Echinacea (Angustifolia) 3X, Lomatium Dissectum 3X, Myrrha 3X, Nasturtium Aquaticum 3X, Tabebuia Impetiginosa 3X, Hydrastis Canadensis 5X, Propolis 6X, Bryonia (Alba) 12X, Eupatorium Perfoliatum 12X, Ferrum Phosphoricum 12X, Gelsemium Sempervirens 12X, Ipecacuanha 12X, Mercurius Corrosivus 12X, Pyrogenium 30X, 60X, 200X, Influenzinum (2020-2021) 10C, 30C, 200C.

INDICATIONS:

For temporary relief of minor aches and pains in muscles and joints, fever with dryness of mucous membranes and dry cough; muscular soreness and fatigue with headache.

WARNINGS:

If pregnant or breast-feeding, ask a health care professional before use.

Keep out of reach of children. In case of overdose, get medical help or contact a Poison Control Center right away.

Do not use if tamper evident seal is broken or missing.

Store in a cool, dry place.

Keep out of reach of children. In case of overdose, get medical help or contact a Poison Control Center right away.

DIRECTIONS:

10 drops orally, 3 times a day. Consult a physician for use in children under 12 years of age.

INDICATIONS:

For temporary relief of minor aches and pains in muscles and joints, fever with dryness of mucous membranes and dry cough; muscular soreness and fatigue with headache.

INACTIVE INGREDIENTS:

Demineralized Water, 25% Ethanol

QUESTIONS:

Distributed by:

BioActive Nutritional, Inc.

1803 N. Wickham Rd.

Melbourne, FL 32935

bioactivenutritional.com

PACKAGE LABEL DISPLAY:

BIOActive Nutritional
RESPIFORCE I
HOMEOPATHIC
1 FL OZ (30 ml)